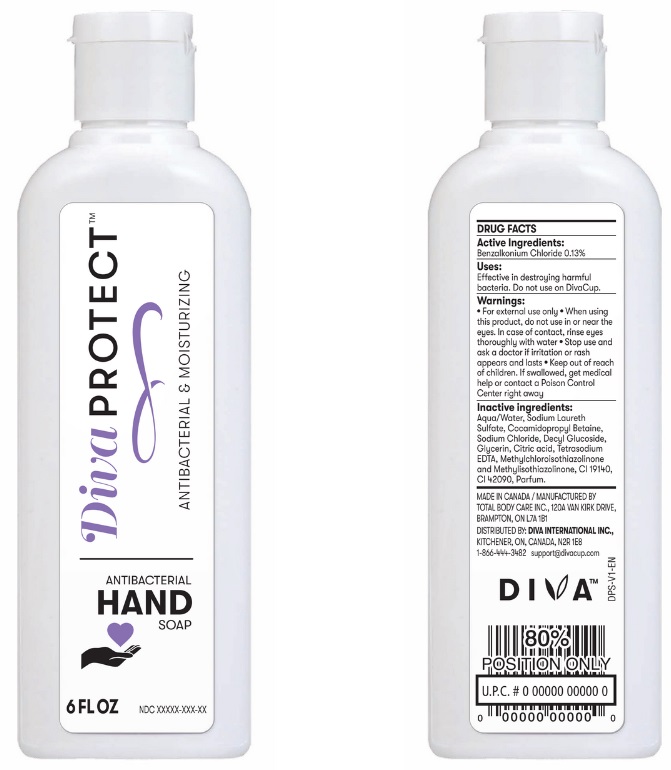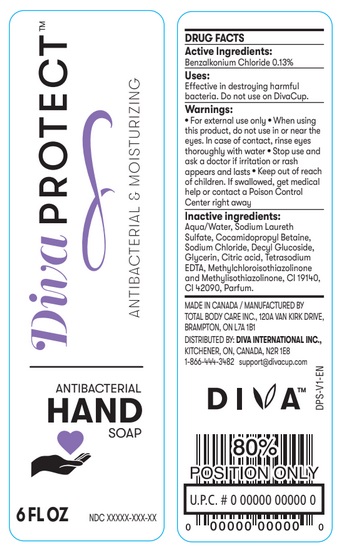 DRUG LABEL: DIVAPROTECT Hand Sanitizer
NDC: 77116-002 | Form: LIQUID
Manufacturer: Diva International Inc.
Category: otc | Type: HUMAN OTC DRUG LABEL
Date: 20200501

ACTIVE INGREDIENTS: BENZALKONIUM CHLORIDE 1.3 mg/1 mL
INACTIVE INGREDIENTS: WATER; SODIUM LAURETH SULFATE; COCAMIDOPROPYL BETAINE; SODIUM CHLORIDE; DECYL GLUCOSIDE; GLYCERIN; ANHYDROUS CITRIC ACID; EDETATE SODIUM; METHYLCHLOROISOTHIAZOLINONE/METHYLISOTHIAZOLINONE MIXTURE

Active ingredient

Benzalkonium Chloride 0.13%

Uses

Effective in destroying harmful bacteria. Do not use on DivaCup.

Warnings

- For external use only.
- When using this product, do not use in or near the eyes. In case of contact, rinse eyes thoroughly with water.
- Stop use and ask a doctor if irritation or rash appears and lasts.

Keep out of reach of children. If swallowed, get medical help or contact a Poison Control Center right away.

Inactive ingredients

Aqua/Water, Sodium Laureth Sulfate, Cocamidopropyl Betaine, Sodium Chloride, Decyl Glucoside, Glycerin, Citric acid, Tetrasodium EDTA, Methylchloroisothiazolinone and Methylisothiazolinone, CI 19140, CI 42090, Parfum.